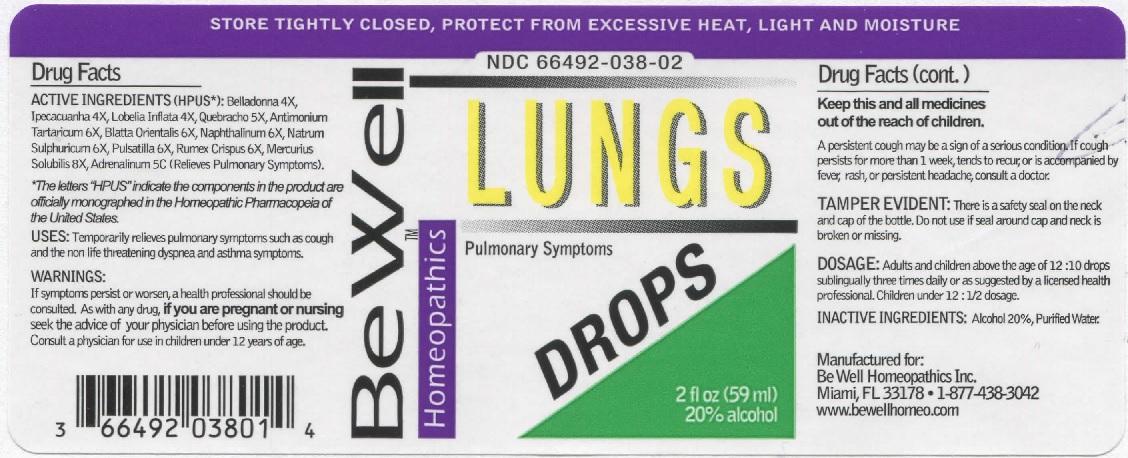 DRUG LABEL: Lung Drops
NDC: 66492-038 | Form: LIQUID
Manufacturer: Be Well Medical dba Richard Clement Nutrition y Be Well Homeopathics
Category: homeopathic | Type: HUMAN OTC DRUG LABEL
Date: 20211229

ACTIVE INGREDIENTS: ATROPA BELLADONNA 4 [hp_X]/59 mL; IPECAC 4 [hp_X]/59 mL; LOBELIA INFLATA 4 [hp_X]/59 mL; ASPIDOSPERMA QUEBRACHO-BLANCO BARK 5 [hp_X]/59 mL; ANTIMONY POTASSIUM TARTRATE 6 [hp_X]/59 mL; BLATTA ORIENTALIS 6 [hp_X]/59 mL; NAPHTHALENE 6 [hp_X]/59 mL; SODIUM SULFATE 6 [hp_X]/59 mL; ANEMONE PULSATILLA 6 [hp_X]/59 mL; RUMEX CRISPUS ROOT 6 [hp_X]/59 mL; MERCURIUS SOLUBILIS 8 [hp_X]/59 mL; EPINEPHRINE 5 [hp_C]/59 mL
INACTIVE INGREDIENTS: ALCOHOL; WATER

Lung Drops

ACTIVE INGREDIENT

ACTIVE INGREDIENTS (HPUS*): Belladonna 4X, Ipecacuanha 4X, Lobelia Inflata 4X, Quebracho 5X, Antimonium Tartaricum 6X, Blatta Orientalis 6X, Naphthalinum 6X, Natrum Sulphuricum 6X, Pulsatilla 6X, Rumex Crispus 6X, Mercurius Solubilis 8X, Adrenalinum 5C (Relieves Pulmonary Symptoms).

*The letters "HPUS" indicate that the components in the product are officially monographed in the Homeopathic Pharmacopeia of the United States.

INDICATIONS AND USAGE

USES: Temporarily relieves pulmonary symptoms such as cough and the non life threatening dyspnea and asthma symptoms.

WARNINGS

WARNINGS: If symptoms persist or worsen, a health professional should be consulted. As with any drug, if you are pregnant or nursing seek the advice of your physician before using this product. Consult a physician for use in children under 12 years of age.

KEEP OUT OF REACH OF CHILDREN

Keep this and all medicines out of the reach of children.

DOSAGE AND ADMINISTRATION

DOSAGE: Adults and children above the age of 12: 10 drops sublingually three times daily or as suggested by a licensed health professional. Children under 12: 1/2 dosage.

OTHER SAFETY INFORMATION

TAMPER EVIDENT: There is a safety seal on the neck and cap of the bottle. Do not use this product if the safety seal is broken or missing.

INACTIVE INGREDIENTS: Alcohol 20%, Purified Water.

QUESTIONS

Manufactured for: Be Well Homeopathics Inc. Miami, FL 33178 • 1-877-438-3042

www.bewellhomeo.com

PACKAGE LABEL

STORE TIGHTLY CLOSED, PROTECT FROM EXCESSIVE HEAT, LIGHT AND MOISTURE

NDC 66492-038-02

Be Well Homeopathics

LUNGS DROPS

2 fl oz (59 ml) 20% alcohol

PURPOSE

Pulmonary Symptoms